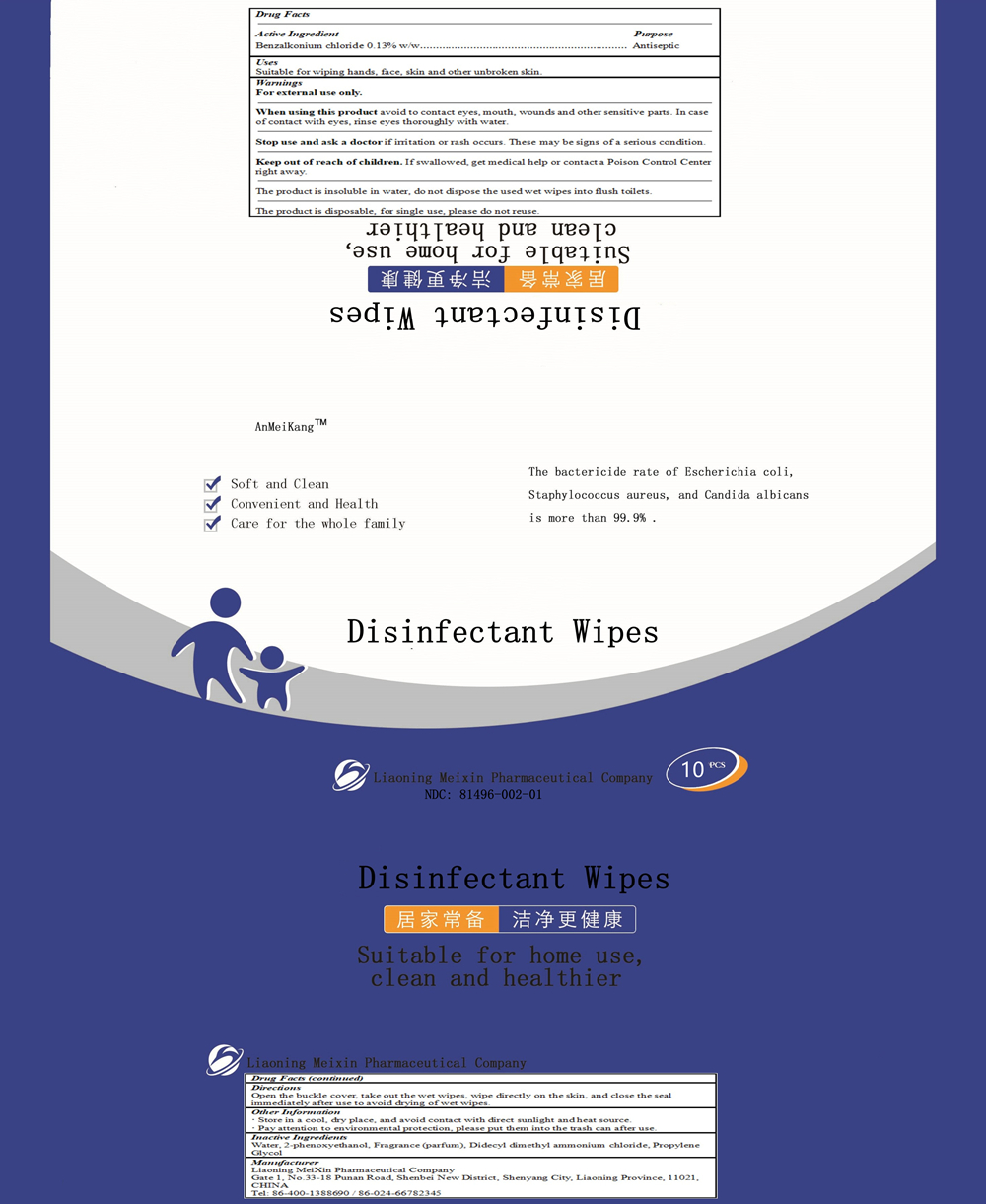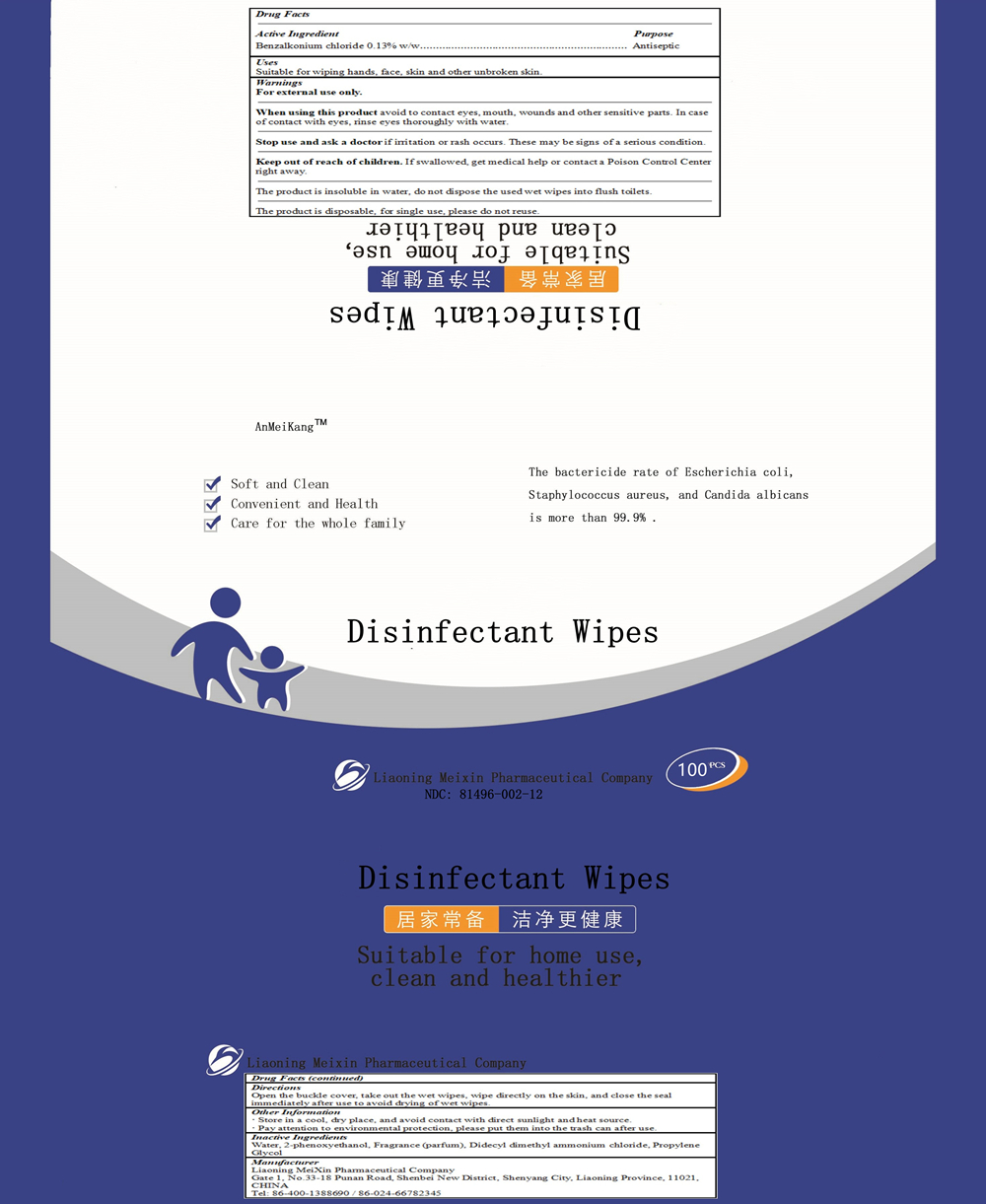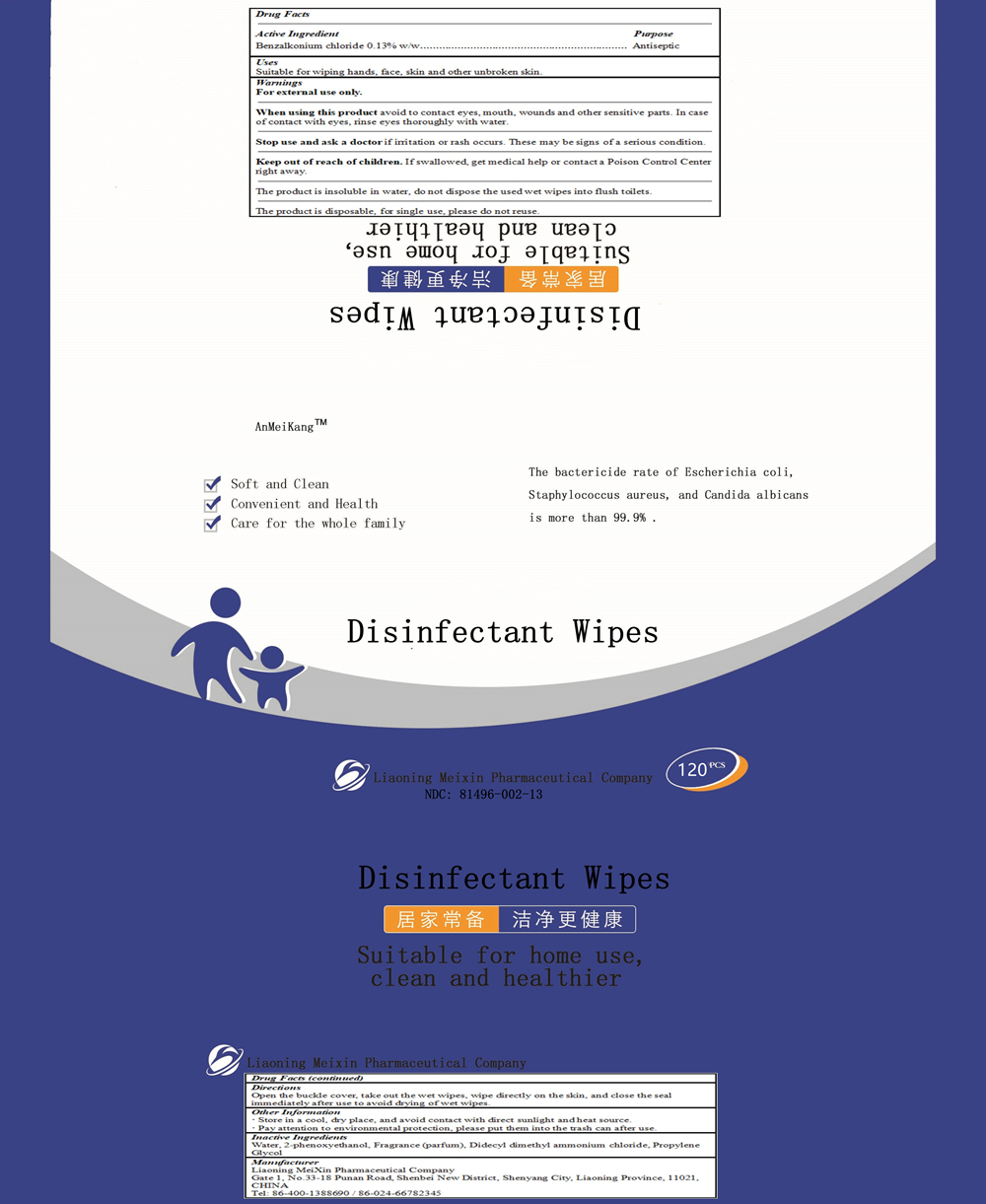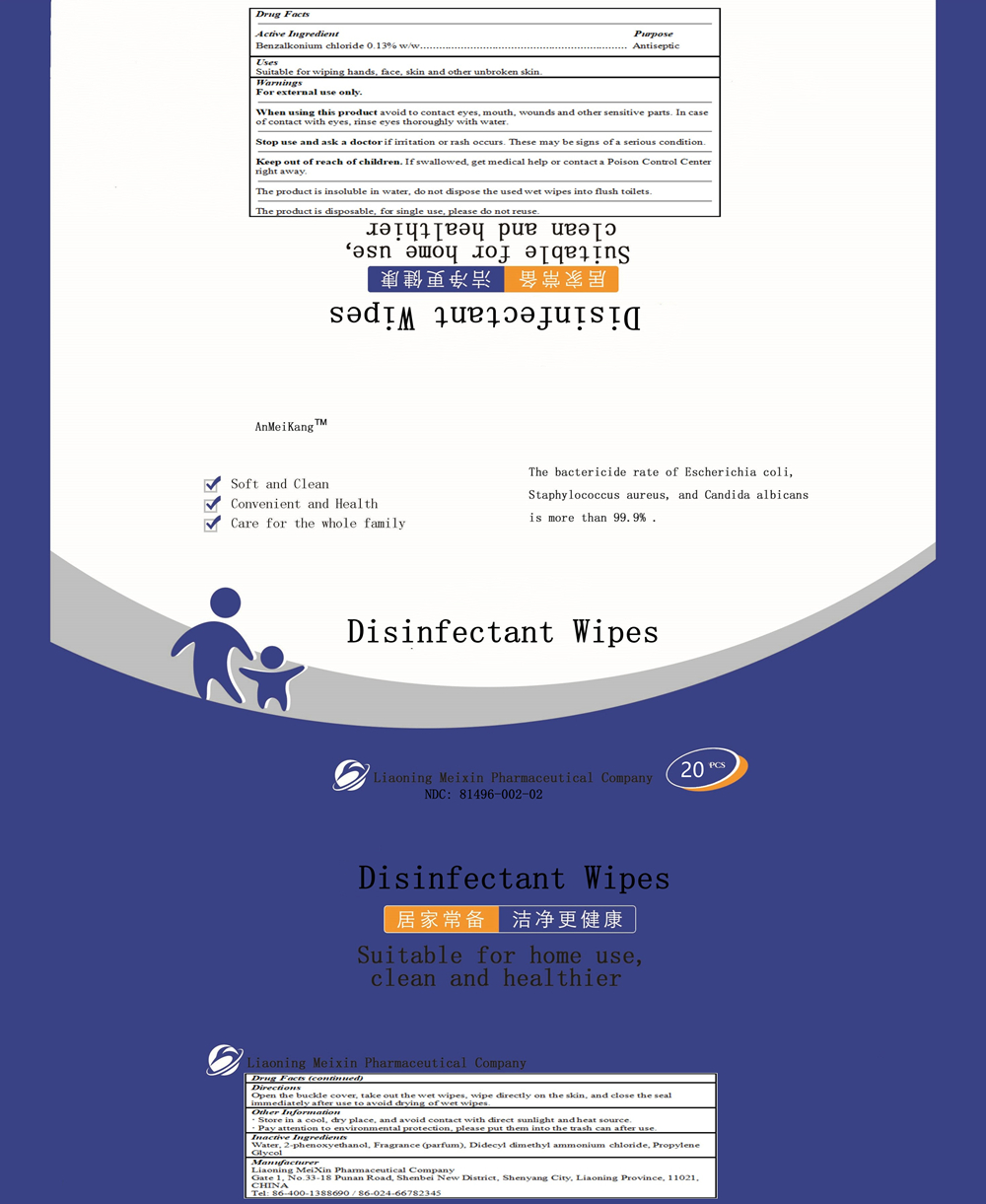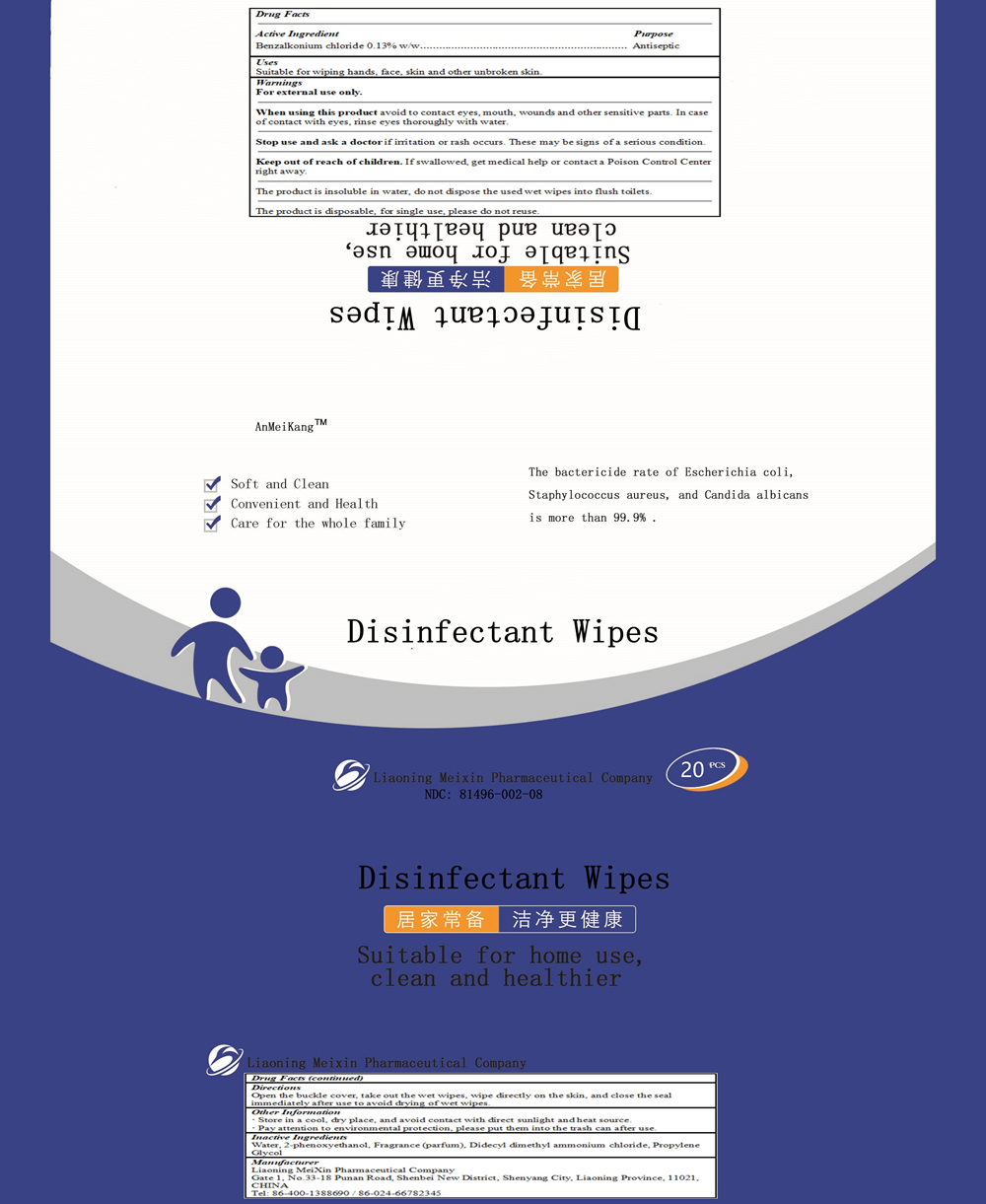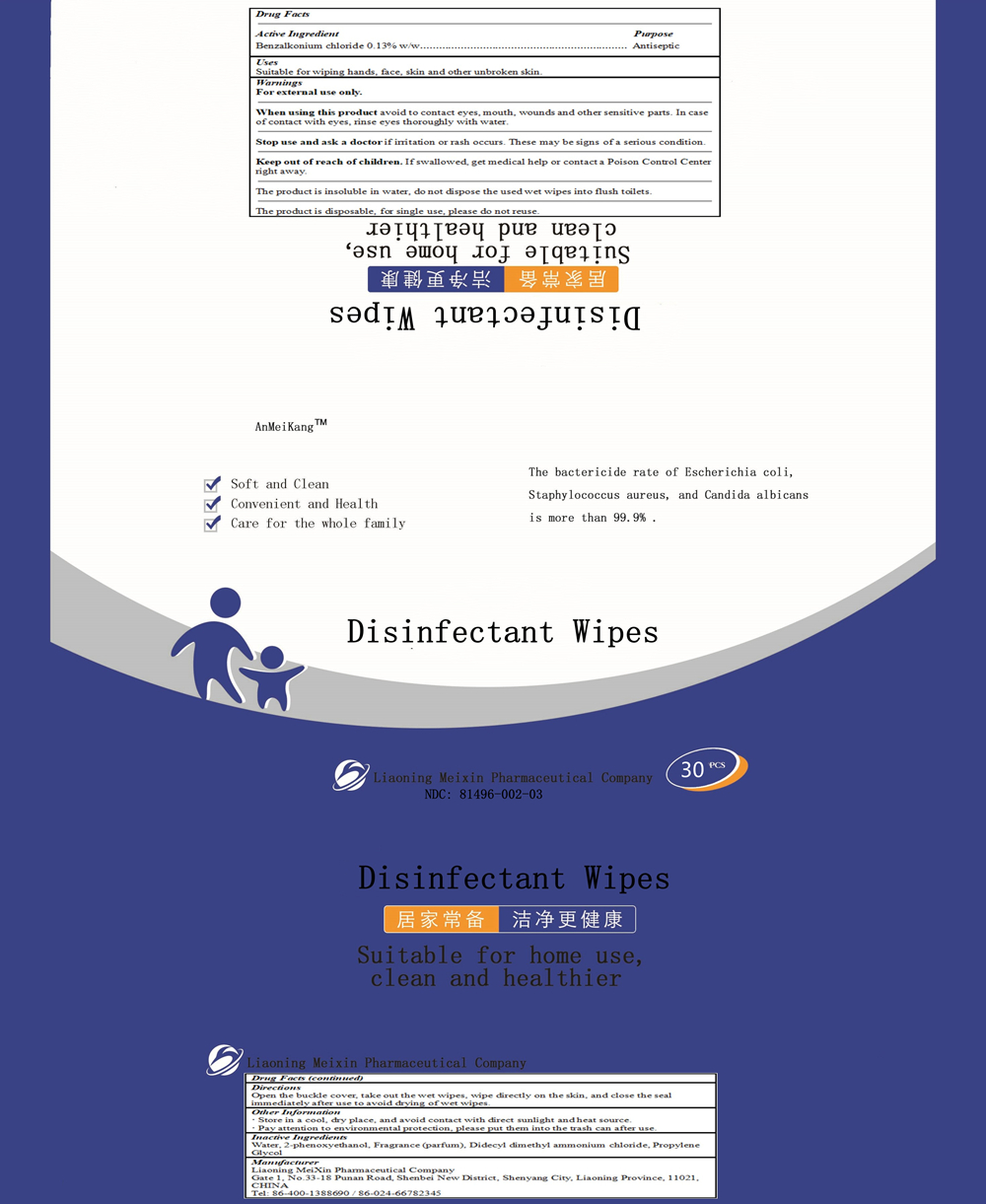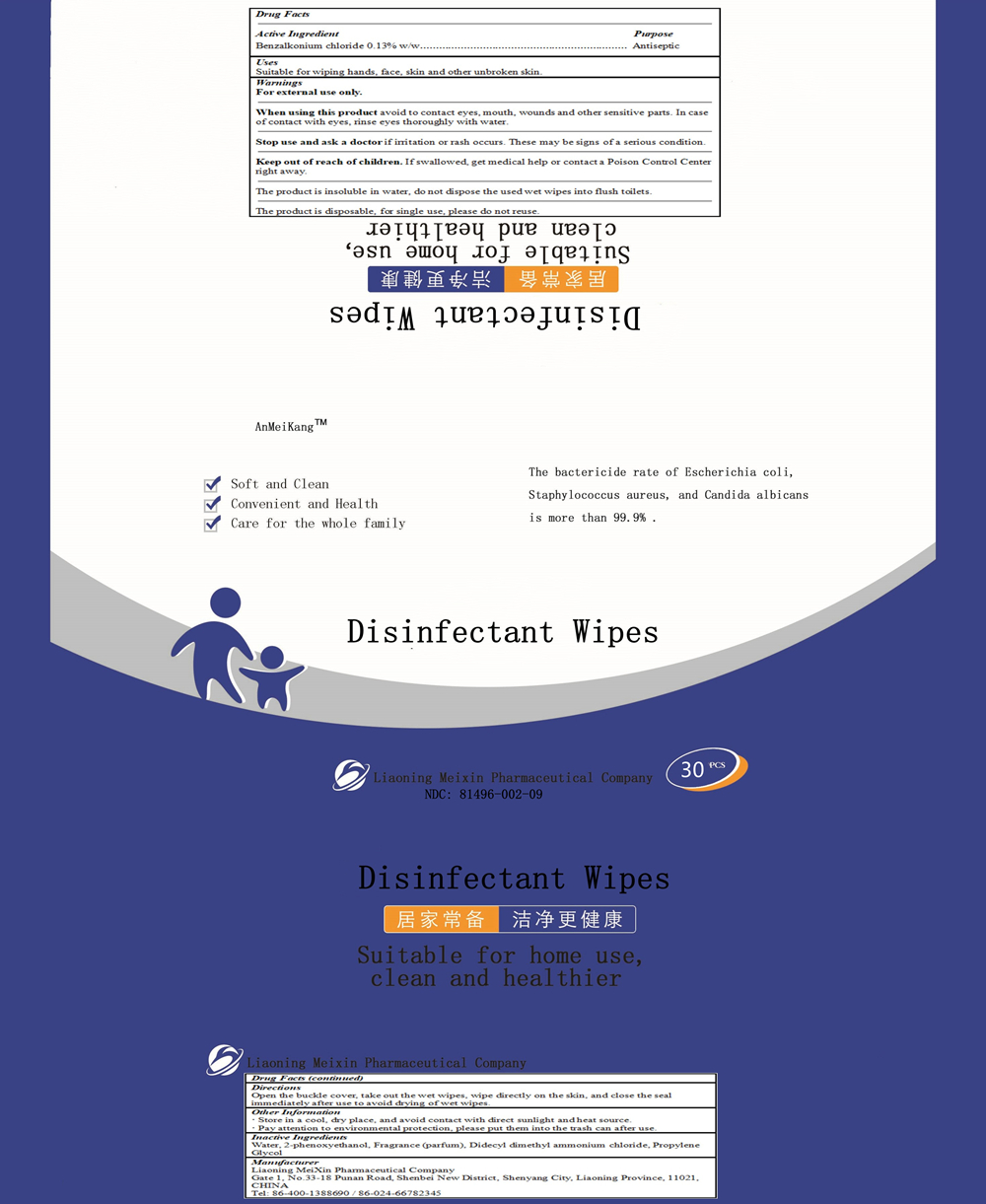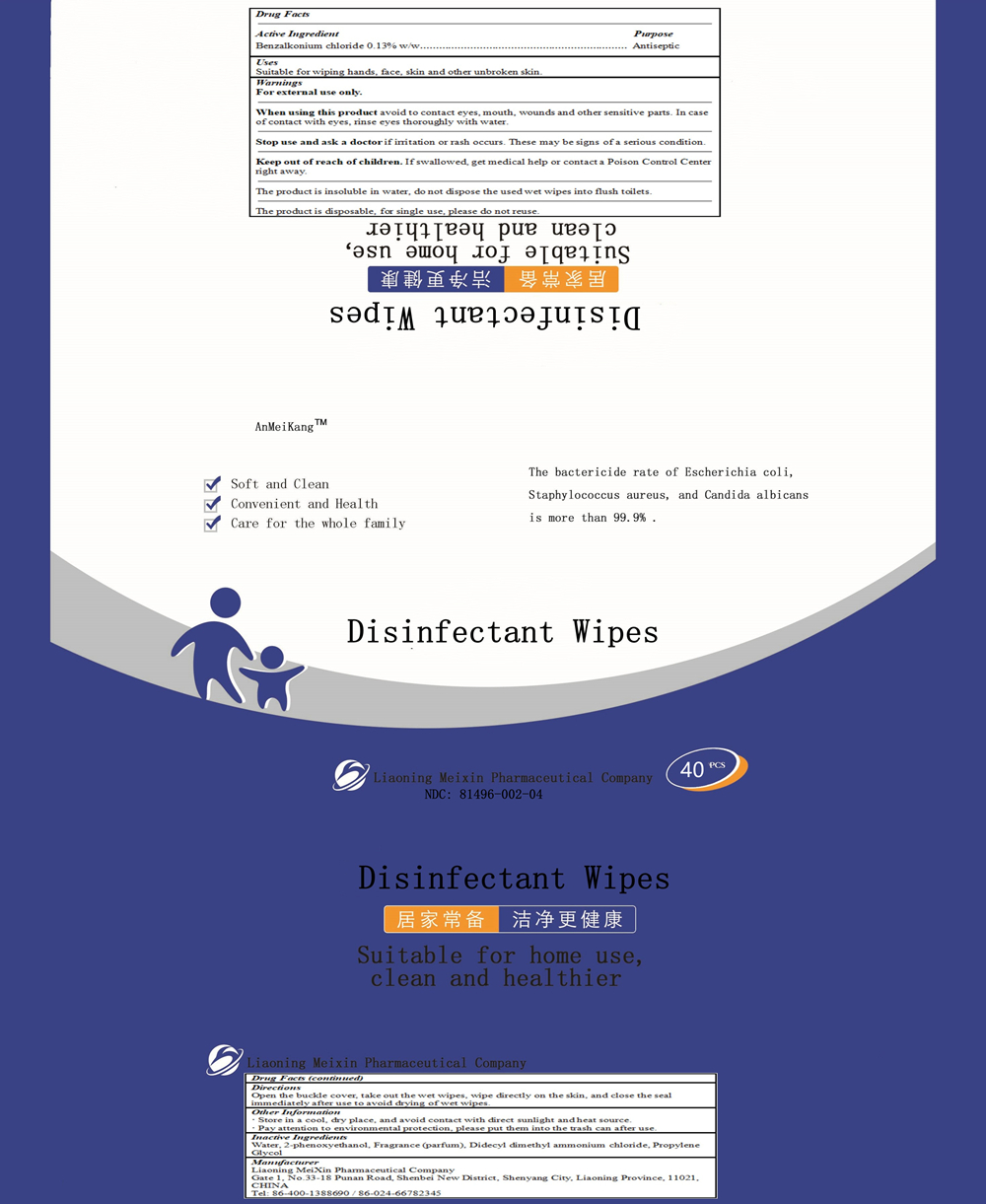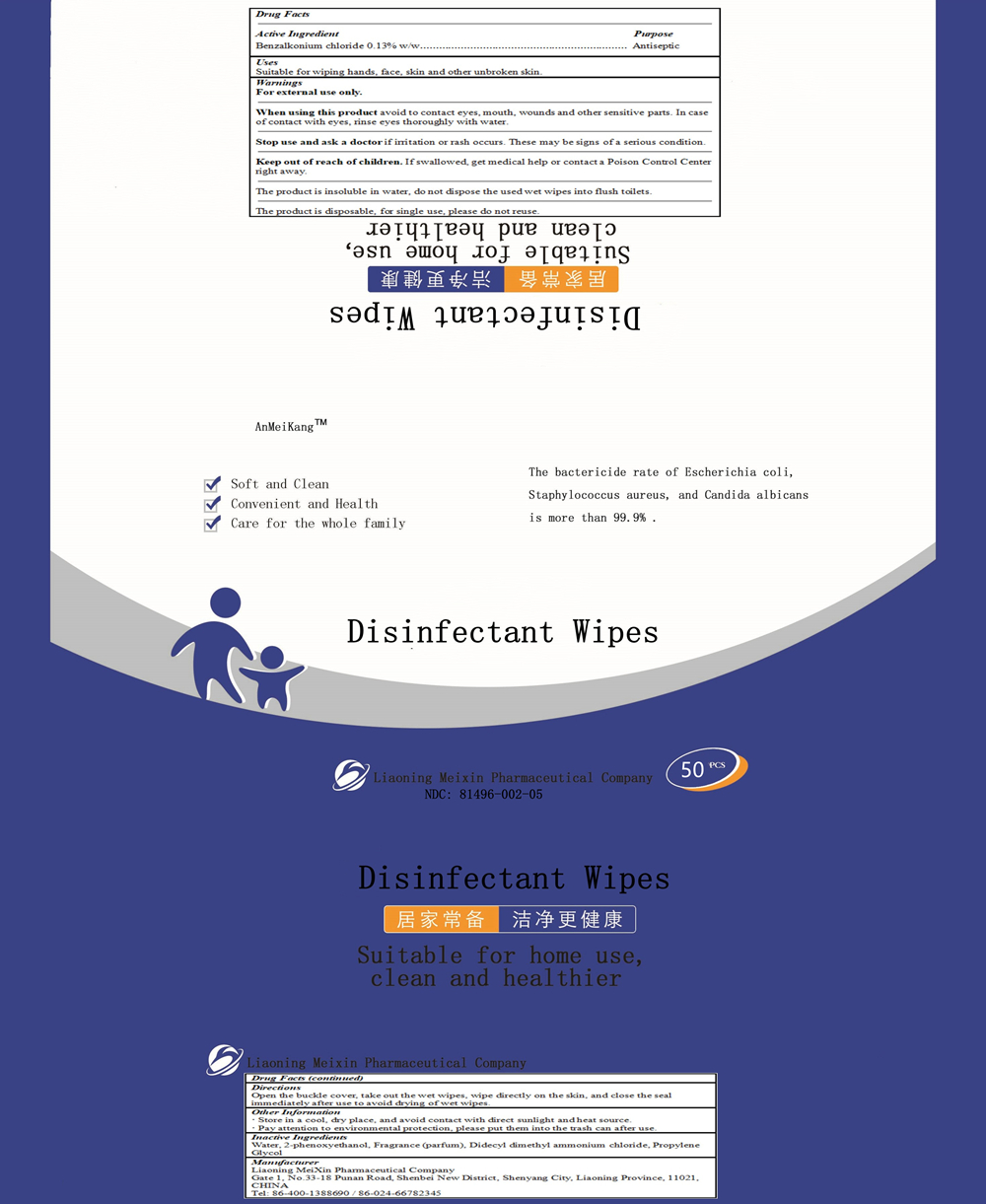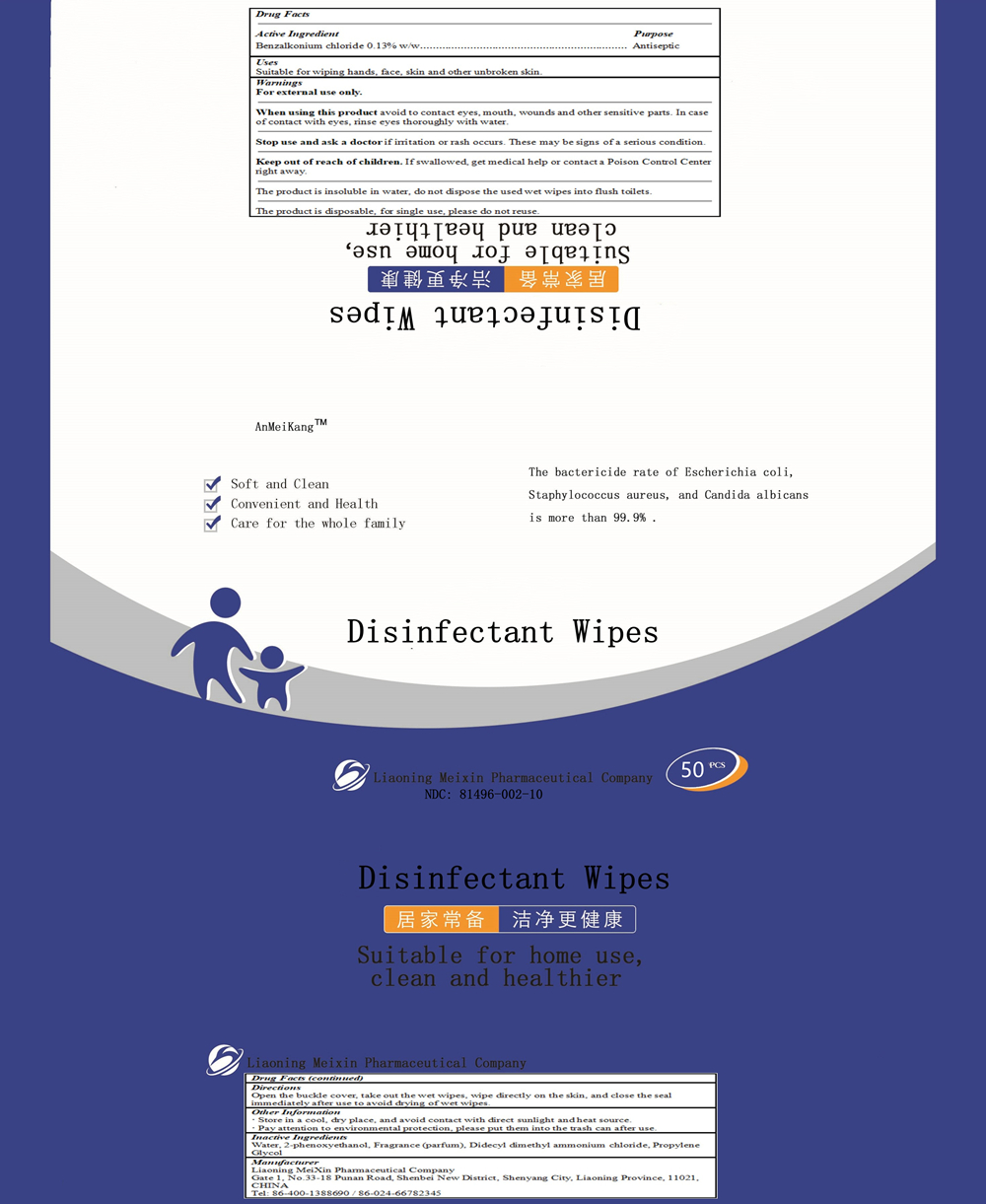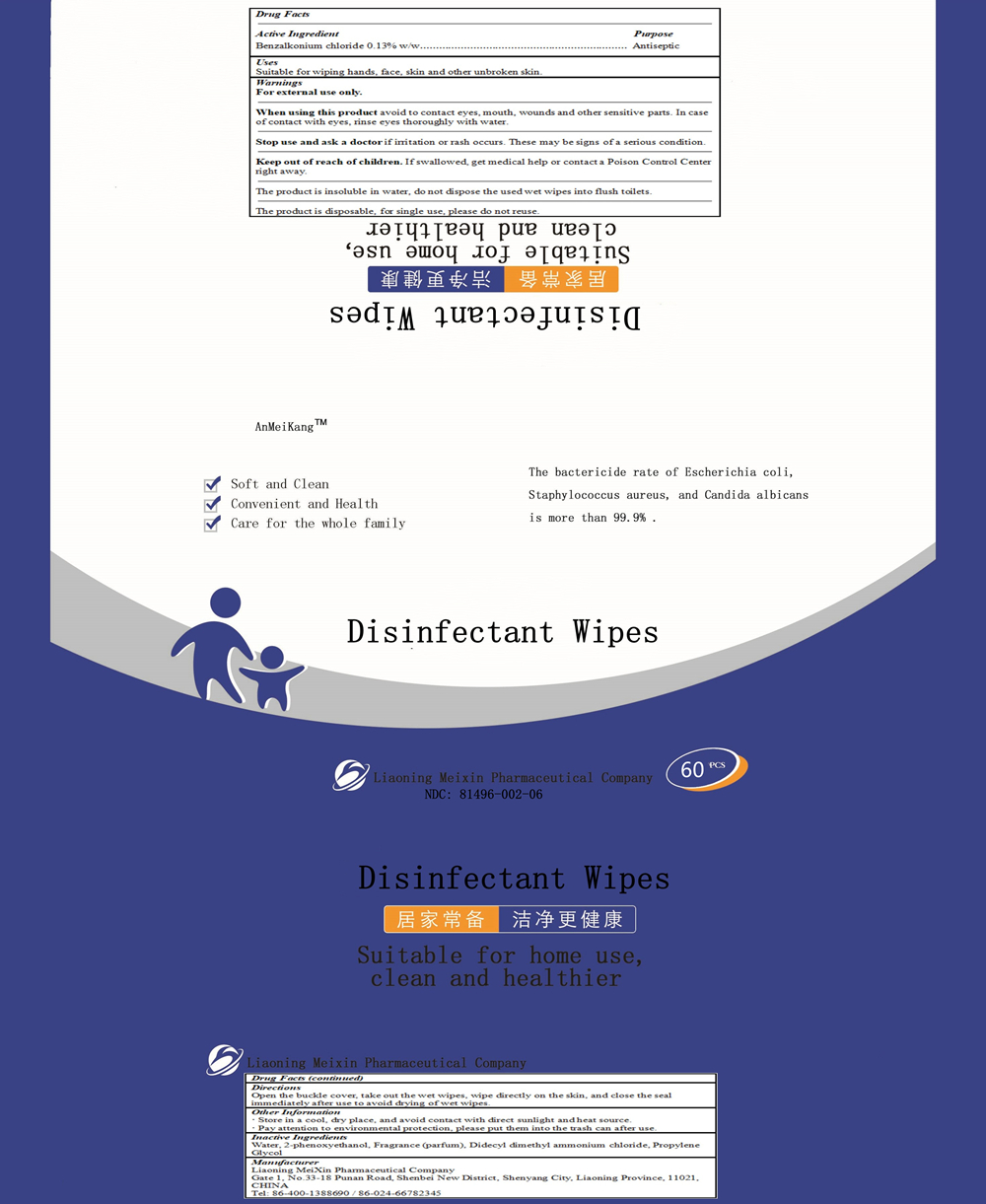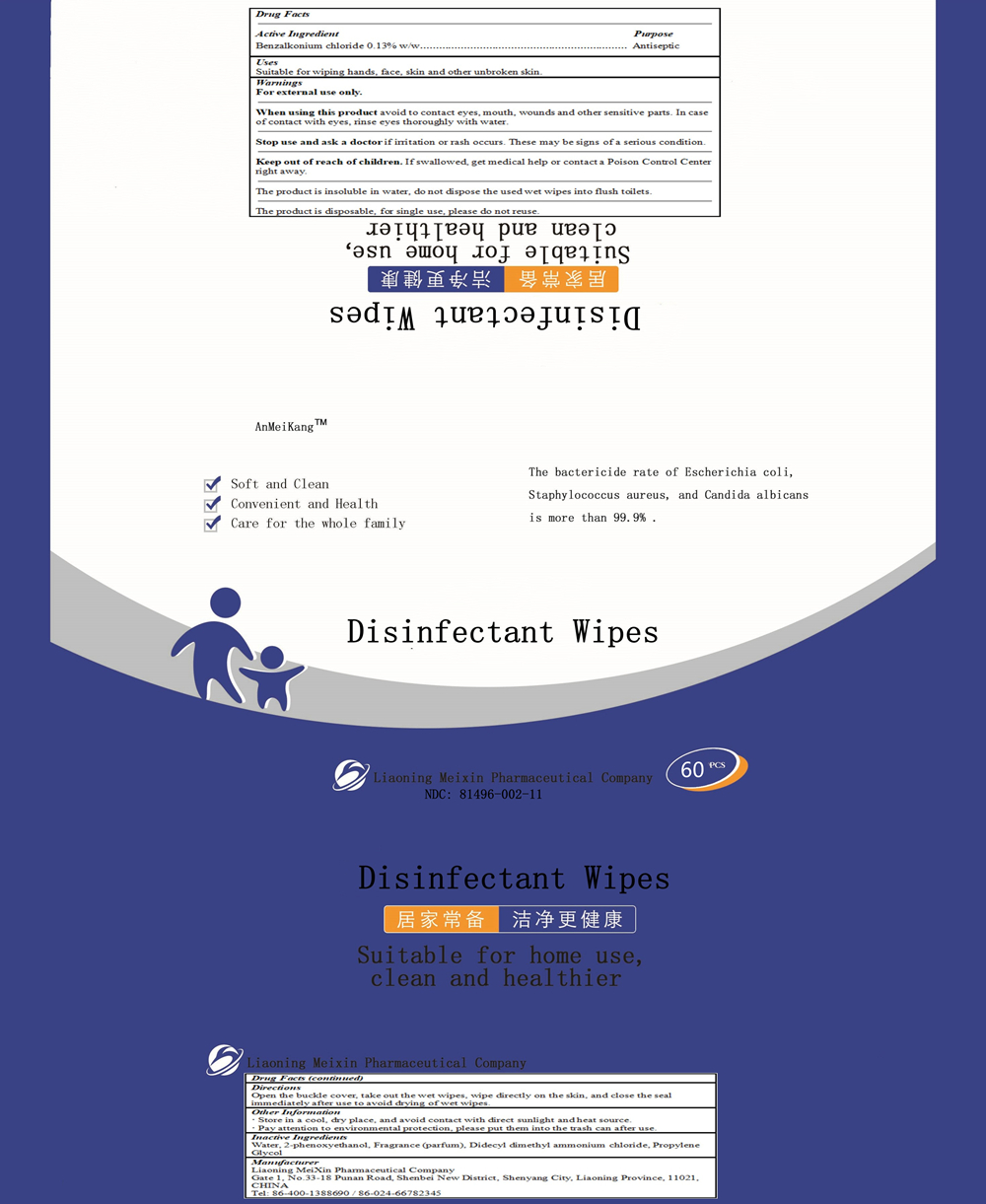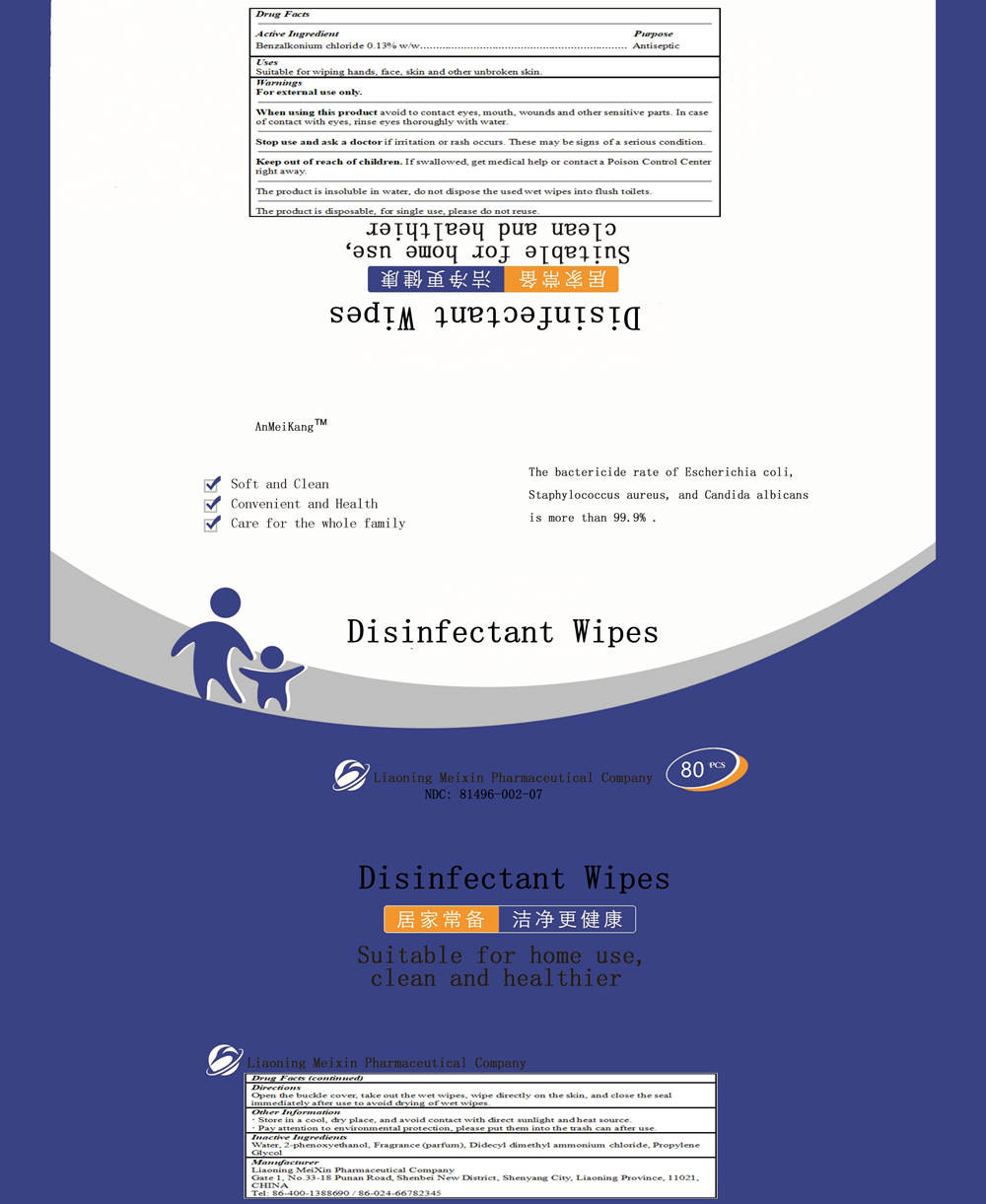 DRUG LABEL: AnMeiKang Disinfectant Wipes
NDC: 81496-002 | Form: CLOTH
Manufacturer: Liaoning MeiXin Pharmaceutical Company
Category: otc | Type: HUMAN OTC DRUG LABEL
Date: 20210326

ACTIVE INGREDIENTS: BENZALKONIUM CHLORIDE 0.13 g/100 g
INACTIVE INGREDIENTS: PHENOXYETHANOL; FRAGRANCE CLEAN ORC0600327; WATER; DIDECYLDIMONIUM CHLORIDE; PROPYLENE GLYCOL

AnMeiKang Disinfectant Wipes

Active Ingredient

Benzalkonium chloride 0.13% w/w

Purpose

Antiseptic

Uses

Suitable for wiping hands, face, skin and other unbroken skin.

Warnings

For external use only.

When using this product avoid to contact eyes, mouth, wounds and other sensitive parts. In case of contact with eyes, rinse eyes thoroughly with water.

Stop use and ask a doctor if irritation or rash occurs. These may be signs of a serious condition.

Keep out of reach of children. If swallowed, get medical help or contact a Poison Control Center right away.

The product is insoluble in water, do not dispose the used wet wipes into flush toilets.

The product is disposable, for single use, please do not reuse.

Directions

Open the buckle cover, take out the wet wipes, wipe directly on the skin, and close the seal immediately after use to avoid drying of wet wipes.

Other Information

· Store in a cool, dry place, and avoid contact with direct sunlight and heat source.

· Pay attention to environmental protection, please put them into the trash can after use.

Keep out of reach of children. If swallowed, get medical help or contact a Poison Control Center right away.

Inactive Ingredients

Water, 2-phenoxyethanol, Fragrance (parfum), Didecyl dimethyl ammonium chloride, Propylene Glycol

PACKAGE LABEL

10 PCS in bag, NDC: 81496-002-01

PACKAGE LABEL

20 PCS in bag, NDC: 81496-002-02

PACKAGE LABEL

30 PCS in bag, NDC: 81496-002-03

PACKAGE LABEL

40 PCS in bag, NDC: 81496-002-04

PACKAGE LABEL

50 PCS in bag, NDC: 81496-002-05

PACKAGE LABEL

60 PCS in bag, NDC: 81496-002-06

PACKAGE LABEL

80 PCS in bag, NDC: 81496-002-07

PACKAGE LABEL

20 PCS in box, NDC: 81496-002-08

PACKAGE LABEL

30 PCS in box, NDC: 81496-002-09

PACKAGE LABEL

50 PCS in box, NDC: 81496-002-10

PACKAGE LABEL

60 PCS in canister, NDC: 81496-002-11

PACKAGE LABEL

100 PCS in canister, NDC: 81496-002-12

PACKAGE LABEL

120 PCS in canister, NDC: 81496-002-13